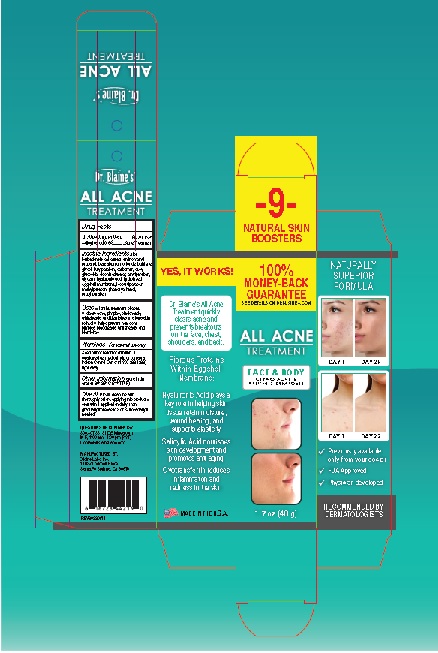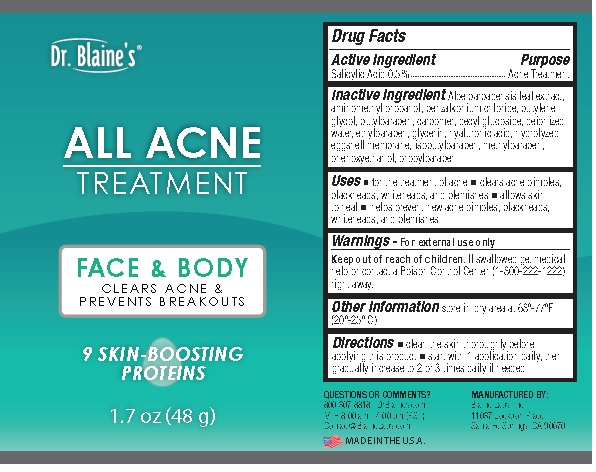 DRUG LABEL: All Acne Treatment
NDC: 63347-130 | Form: GEL
Manufacturer: Blaine Labs Inc.
Category: otc | Type: HUMAN OTC DRUG LABEL
Date: 20231221

ACTIVE INGREDIENTS: SALICYLIC ACID 0.5 g/100 g
INACTIVE INGREDIENTS: ALOE VERA LEAF; AMINOMETHYLPROPANOL; BENZALKONIUM CHLORIDE; BUTYLENE GLYCOL; BUTYLPARABEN; CARBOMER HOMOPOLYMER, UNSPECIFIED TYPE; DECYL GLUCOSIDE; WATER; ETHYLPARABEN; GLYCERIN; HYALURONIC ACID; EGG SHELL MEMBRANE; ISOBUTYLPARABEN; METHYLPARABEN; PHENOXYETHANOL; PROPYLPARABEN

Dr. Blaine's® All Acne Treatment

Drug Facts

Active Ingredient Salycilic Acid 0.5%

Purpose

Acne Treatment

INDICATIONS AND USAGE

Uses ■ for the treatment of acne

■ clears acne pimples, blackheads,

whiteheads and blemishes ■ allows skin

to heal ■ helps prevent new acne

pimples, blackheads whiteheads, and

acne blemishec

Warnings - For external use only

Keep out of reach of children. If

swallowed get medical help or contact a

Poison Control Center (1-800-222-1222)

right away.

Other Information store in dry
area at 20º-25º C (68º-77º F)

DOSAGE AND ADMINISTRATION

Directions ■ clean the skin

thoroughly before applying this product

■ start with1 application daily, then

gradually increase to 2 to 3 times daily if

needed

QUESTIONS OR COMMENTS?

800.307.8818 | DrBlaines.com

M-F, 8:00 am - 4:00 pm (PST)

Contact@BlaineLabs.com

Inactive Ingredients Aloe
barbadensis leaf extract, aminomethyl
propanol, benzalkonium chloride, butylene
glycol, butylparaben, carbomer, decyl
glucoside, deionized water, ethylparaben,
glycerin, hyaluronic acid, hydrolyzed
eggshell membrane, isobutylparaben,
methylparaben, phenoxyethanol,
propylparaben

Product Label

Dr. Blaine's®

ALL ACNE

TREATMENT

FACE & BODY

CLEARS ACNE &
PREVENTS BREAKOUTS

1.7 OZ (48 g)

MANUFACTURED BY:
Blaine Labs, Inc.
11037 Lockport Place
Santa Fe Springs, CA 90670

res